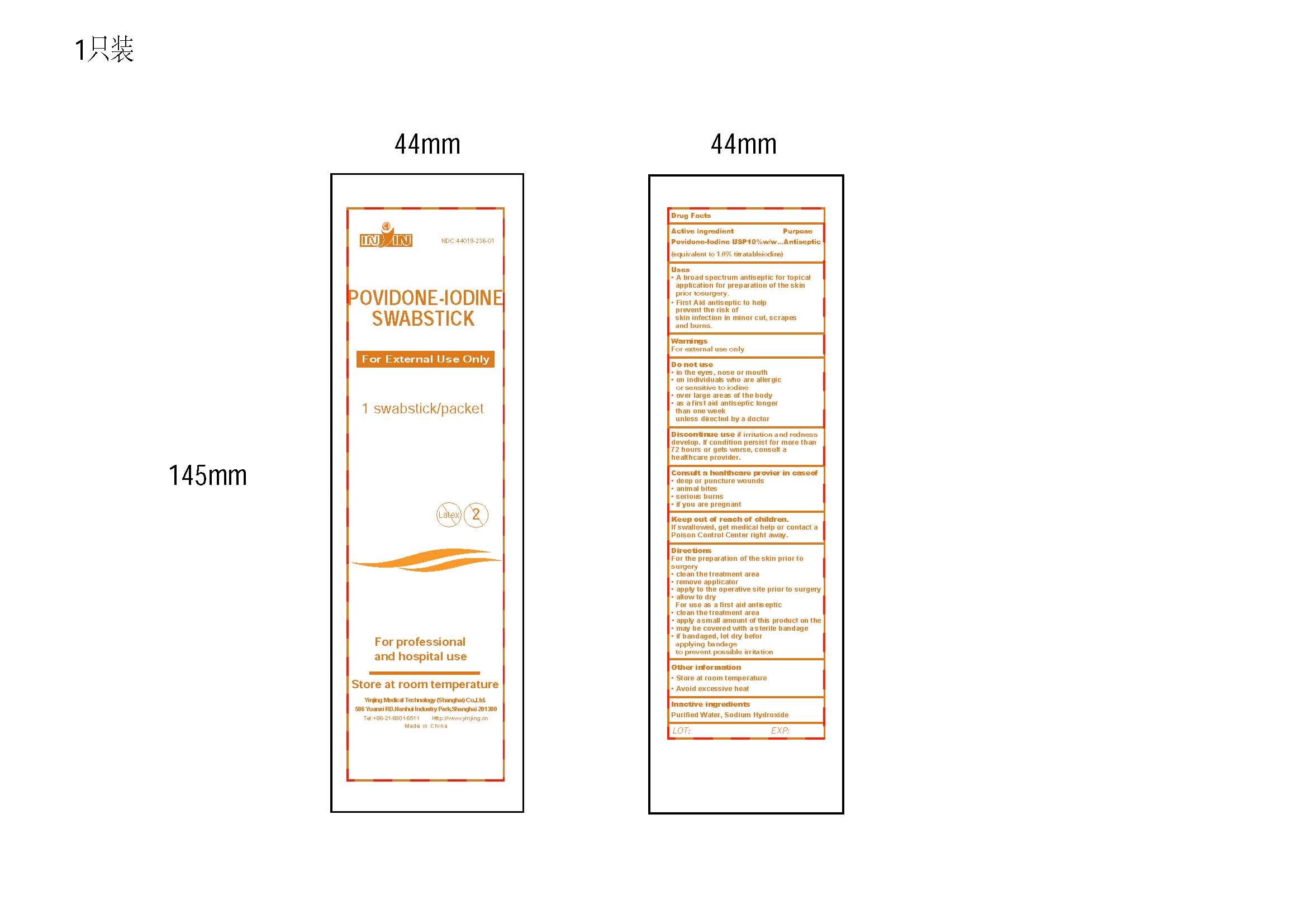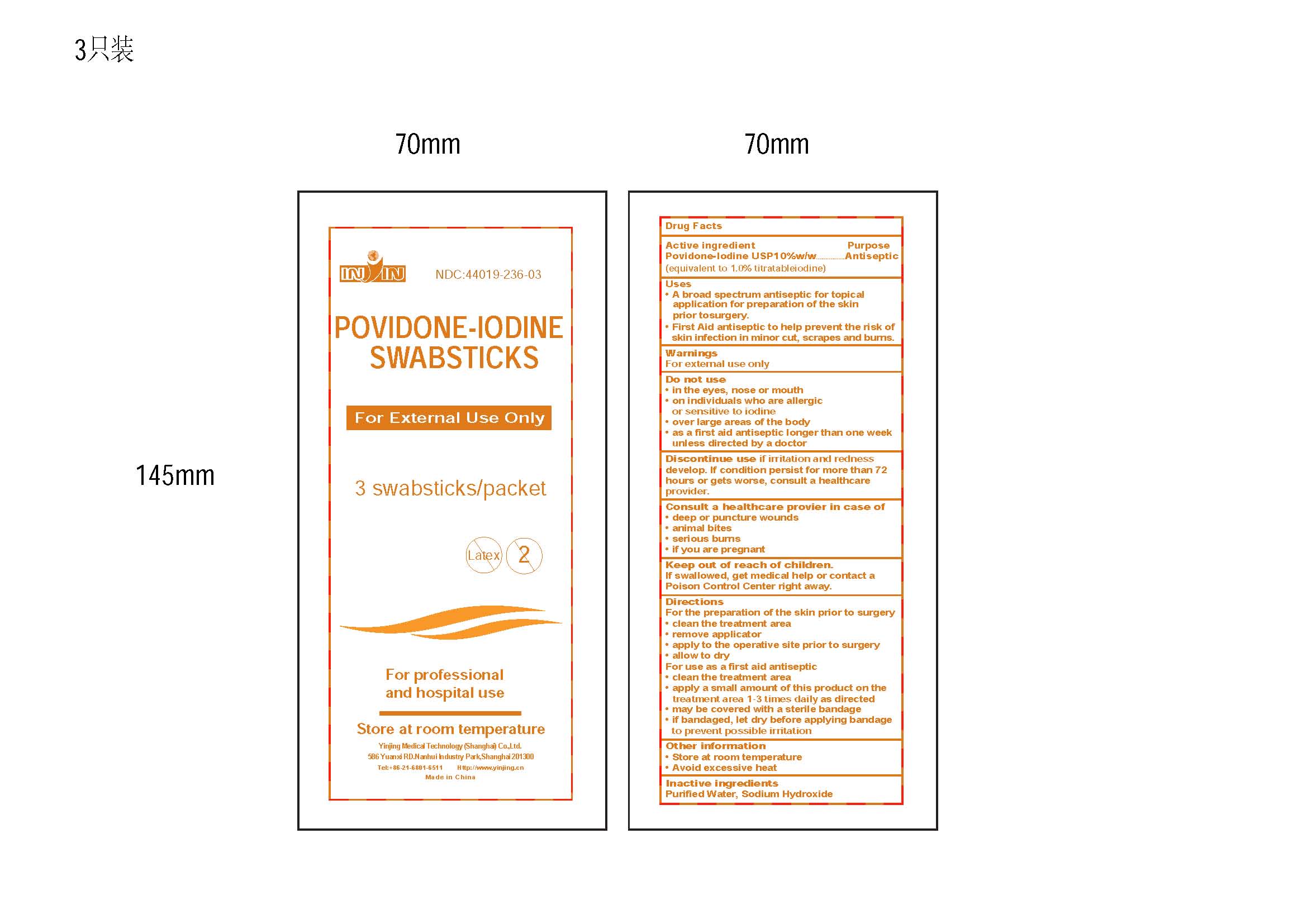 DRUG LABEL: POVIDONE IODINE
NDC: 44019-236 | Form: SWAB
Manufacturer: Yinjing Medical Technology (Shanghai) Co., Ltd.
Category: otc | Type: HUMAN OTC DRUG LABEL
Date: 20171230

ACTIVE INGREDIENTS: POVIDONE-IODINE 10 g/100 g
INACTIVE INGREDIENTS: SODIUM HYDROXIDE; WATER

POVIDONE-IODINE SWABSTICK

Active Ingredients

Povidone-Iodine 10% w/w
(1% titratable iodine)

Purpose

Antiseptic

Use

First aid antiseptic to help prevent infection in scrapes, minor cuts and burns Antiseptic to prepare skin prior to surgery. Uses antiseptic skin preparation

Stop Use Section

Stop use and ask a doctor if skin irritation, redness, swelling, or pain occurs.

Warnings Section

Warnings • Do not use if allergic to iodine • For external use only • Do not use in eyes • Avoid pooling beneath patient • In case of accidental ingestion, seek professional assistance or consult a poison control center immediately.

Keep Out of Reach of Children Section

Keep out of reach of children.

Directions Section

Directions apply locally as needed

Inactive Ingredients Section

Inactive ingredients Sodium hydroxide, water

Other Information Section

Other information
For Hospital or Professional Use Only.
Store at room temperature: 15℃- 30 ℃

For professional and hospital use
Store at room temperature
LOT EXP.

PACKAGE LABEL

IN IN
NDC:44019-236-01
POVIDONE-IODINE SWABSTICK
For External Use Only

1 swabstick/packet